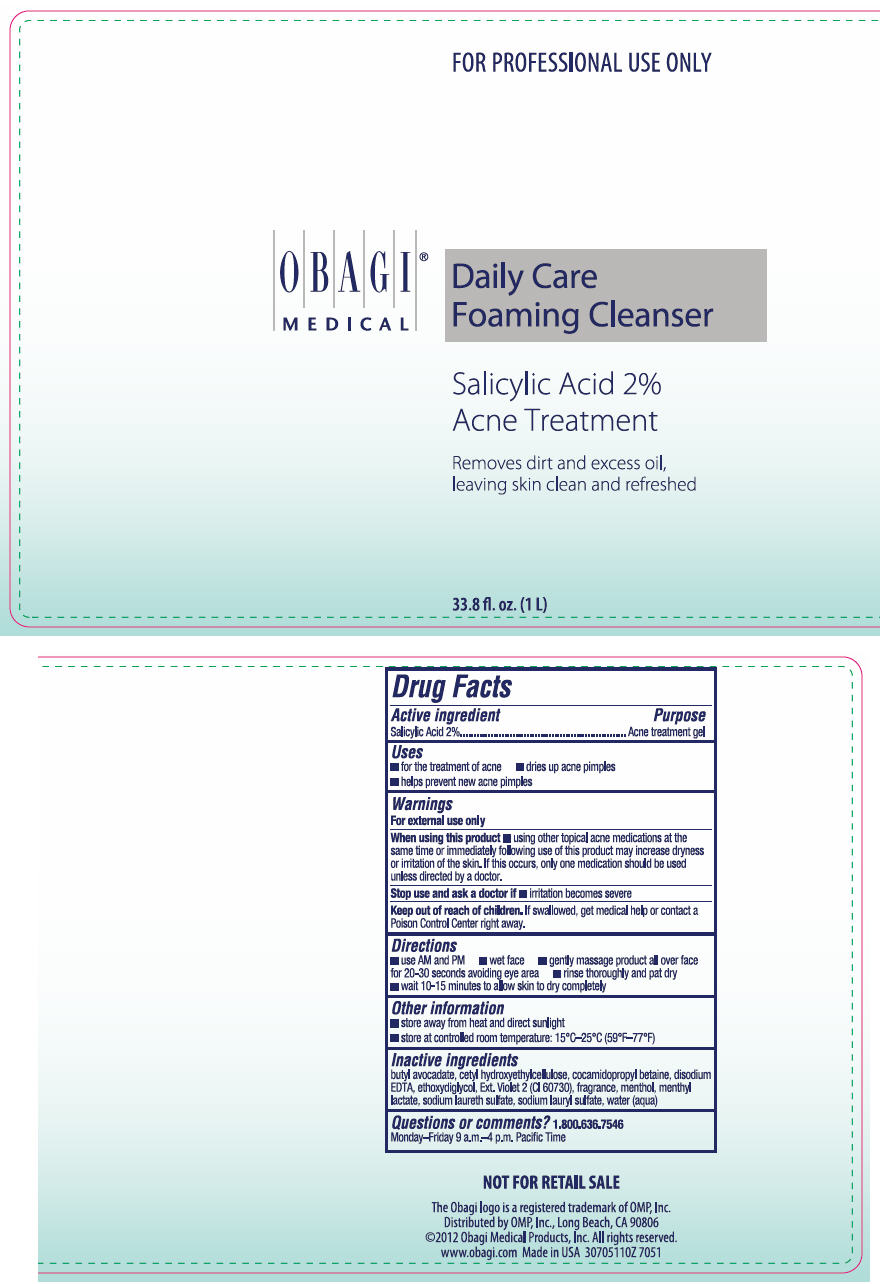 DRUG LABEL: DAILY CARE FOAMING CLEANSER 
NDC: 62032-129 | Form: LIQUID
Manufacturer: OMP, INC.
Category: otc | Type: HUMAN OTC DRUG LABEL
Date: 20130320

ACTIVE INGREDIENTS: SALICYLIC ACID 20 mg/1 mL
INACTIVE INGREDIENTS: SODIUM LAURETH-3 SULFATE; DIETHYLENE GLYCOL MONOETHYL ETHER; SODIUM LAURYL SULFATE; WATER; COCAMIDOPROPYL BETAINE; CETYL HYDROXYETHYLCELLULOSE (350000 MW); EDETATE DISODIUM; MENTHOL; MENTHYL LACTATE, (-)-; EXT. D&C VIOLET NO. 2

DAILY CARE FOAMING CLEANSER
ACNE TREATMENT

Drug Facts

Active ingredient

Salicylic Acid 2%

Purpose

Acne treatment gel

Uses

- for the treatment of acne
- dries up acne pimples
- helps prevent new acne pimples

Warnings

For external use only

When using this product

- using other topical acne medications at the same time or immediately following use of this product may increase dryness or irritation of the skin. If this occurs, only one medication should be used unless directed by a doctor.

Stop use and ask a doctor if

- irritation becomes severe

Keep out of reach of children. If swallowed, get medical help or contact a Poison Control Center right away.

Directions

- use AM and PM
- wet face
- gently massage product all over face for 20-30 seconds avoiding eye area
- rinse thoroughly and pat dry
- wait 10-15 minutes to allow skin to dry completely

Other information

- store away from heat and direct sunlight
- store at controlled room temperature: 15°C–25°C (59°F–77°F)

Inactive ingredients

butyl avocadate, cetyl hydroxyethylcellulose, cocamidopropyl betaine, disodium EDTA, ethoxydiglycol, Ext. Violet 2 (CI 60730), fragrance, menthol, menthyl lactate, sodium laureth sulfate, sodium lauryl sulfate, water (aqua)

Questions or comments?

1.800.636.7546

Monday–Friday 9 a.m.–4 p.m. Pacific Time

Distributed by OMP, Inc., Long Beach, CA 90806

PRINCIPAL DISPLAY PANEL - 1 L Bottle Label

FOR PROFESSIONAL USE ONLY

OBAGI®
MEDICAL

Daily Care
Foaming Cleanser

Salicylic Acid 2%
Acne Treatment

Removes dirt and excess oil,
leaving skin clean and refreshed

33.8 fl. oz. (1 L)